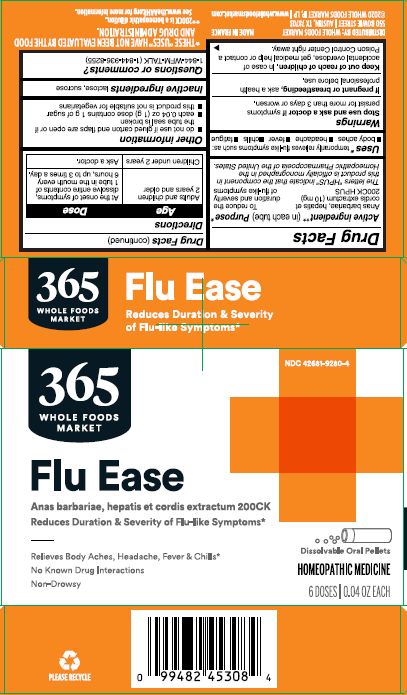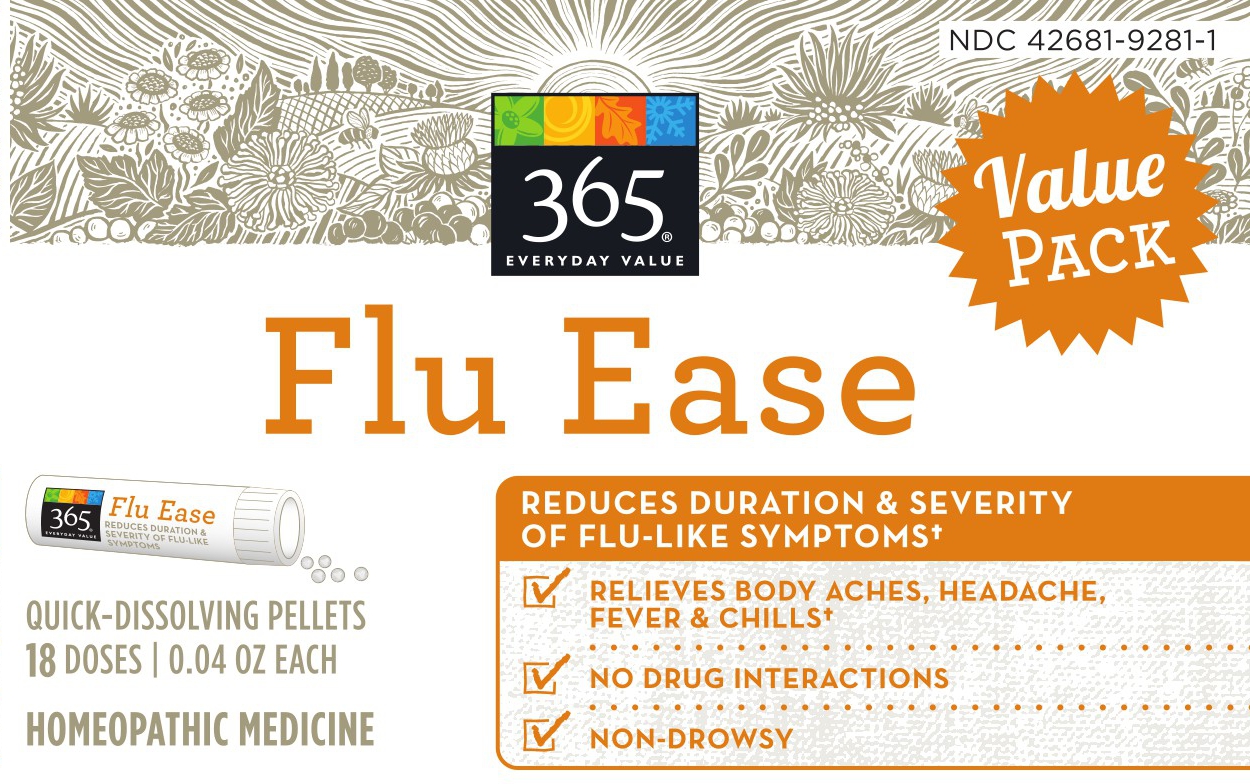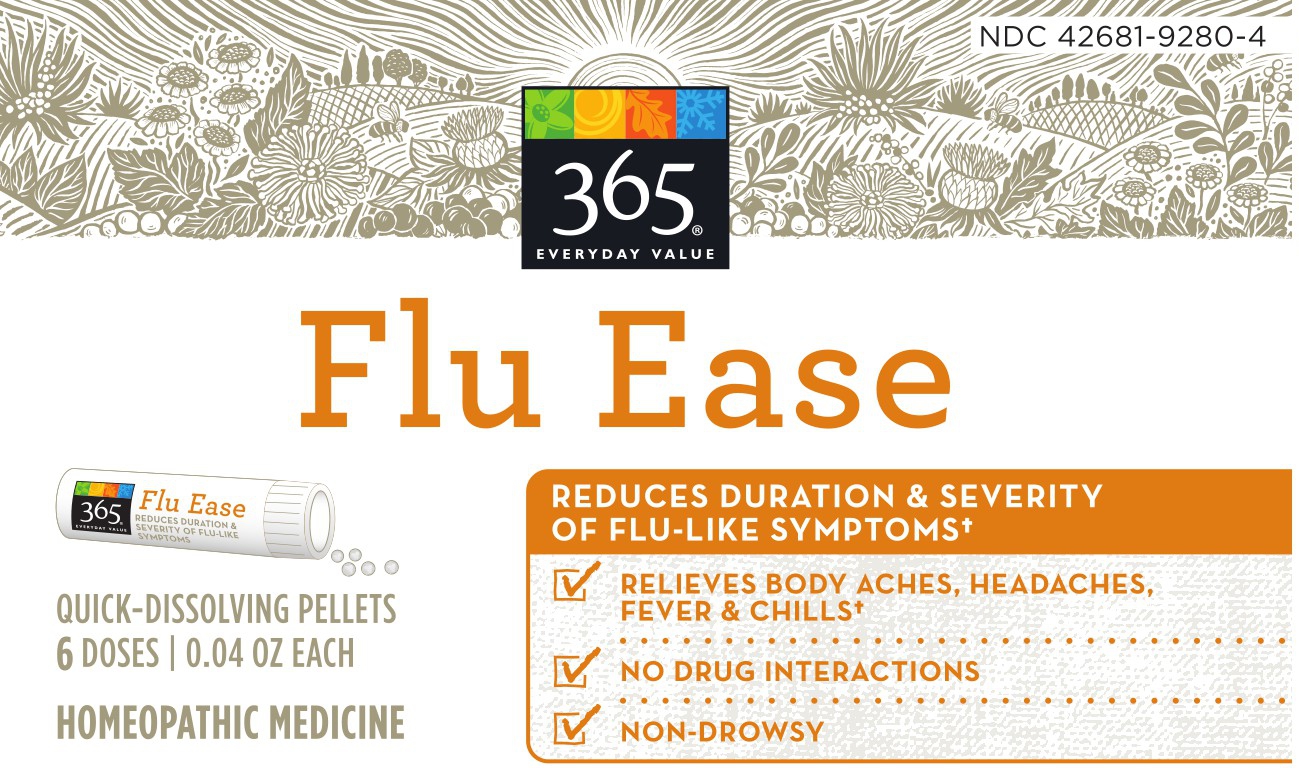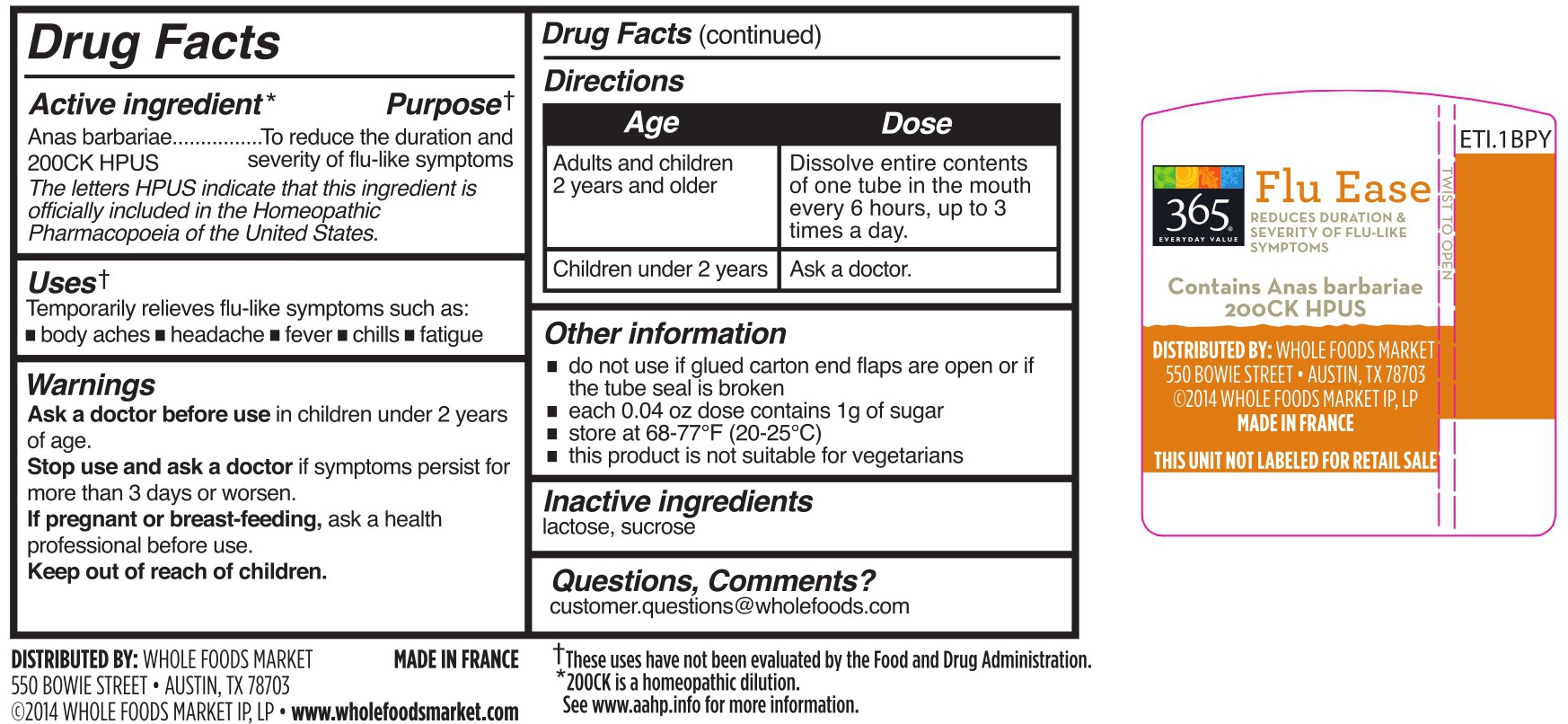 DRUG LABEL: Flu Ease
NDC: 42681-9280 | Form: PELLET
Manufacturer: WFM Private Label, LP
Category: homeopathic | Type: HUMAN OTC DRUG LABEL
Date: 20231004

ACTIVE INGREDIENTS: CAIRINA MOSCHATA HEART/LIVER AUTOLYSATE 200 [hp_C]/1 1
INACTIVE INGREDIENTS: SUCROSE; LACTOSE

Flu Ease

Active Ingredient

Anas barbariae, hepatis et cordis extractum (10mg) 200CK HPUS** (in each tube)

The letters "HPUS" indicate that the component in this product are officially monographed in the Homeopathic Pharmacopoeia of the United States.

Purpose

Anas barbariae | ....... | To reduce the duration and severity of flu-like symptoms.*

Uses

Temporarily relieves flu-like symptoms such as: • body aches • headache • fever • chills • fatigue

WARNINGS

Ask a doctor before use

- in children under 2 years of age

Stop use and ask a doctor

- if symptoms persist for more than 3 days or worsen.

If pregnant or breast-feeding,

- ask a health professional before use.

Keep out of reach of children.

In case of accidental overdose, get medical help or contact a Poison Control Center right away.

Directions

Adults and children 2 years and older: At the onset of symptoms, dissolve entire contents of 1 tube in the mouth every 6 hours, up to 3 times a day.

Children under 2 years: ask a doctor.

Other information

do not use if glued carton end flaps are open or if the tube seal is broken

each 0.04 oz does contains 1g of sugar

this product is not suitable for vegetarians

Relieves Body Aches, Headache, Fever & Chills*

No Known Drug Interactions

Non-Drowsy

18 Doses

6 Doses

Dissolvable Oral Pellets

*THESE "USES" HAVE NOT BEEN EVALUATED BY THE FOOD AND DRUG ADMINISTRATION.

**200CK is a homeopathic dilution. See www.THEAAHP.org for more informaiton.

Distributed by: Whole Foods Market

550 Bowie Street, Austin, TX 78703

© 2020 WHOLE FOODS MARKET IP, LP

www.wholefoodsmarket.com

Made in France

Inactive ingredients

lactose, sucrose

Questions, Comments?

1-844-WFM-TALK (1-844-936-8255)

Principle Display Panel

Drug Facts / Tube

6 dose package

18 dose package